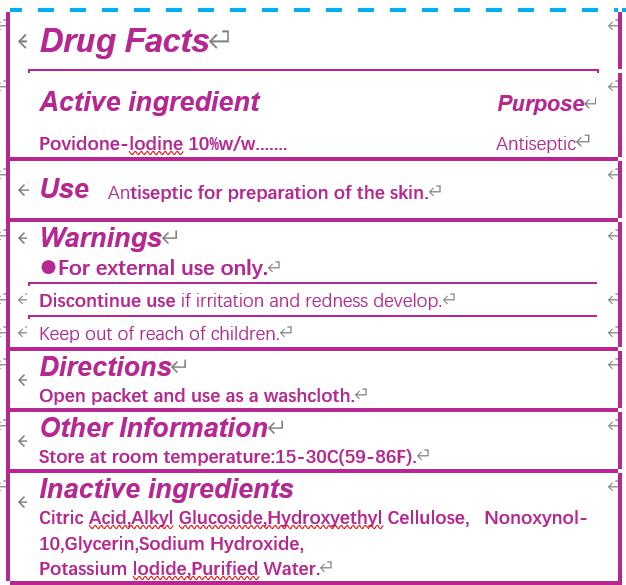 DRUG LABEL: Povidone-iodine prep pad
NDC: 80514-002 | Form: SWAB
Manufacturer: JIANGSU HAIDA INTERNATIONAL TRADING CO., LTD.
Category: otc | Type: HUMAN OTC DRUG LABEL
Date: 20231226

ACTIVE INGREDIENTS: POVIDONE-IODINE 10 g/100 g
INACTIVE INGREDIENTS: GLYCERIN; POTASSIUM IODIDE; HYDROXYETHYL CELLULOSE (100 MPA.S AT 2%); WATER; CITRIC ACID MONOHYDRATE; SODIUM HYDROXIDE; NONOXYNOL-10; C12-20 ALKYL GLUCOSIDE

Active ingredient

Povidone Iodine USP, 10% w/w

Purpose

Antiseptic

CAUTION: Keep out of reach of children

If swallowed, get medical help or contact Poison Control Center right away.

Use

Antiseptic for preparation of the skin.

WARNINGS

For external use only.

Discontinue use if irritation and redness develop.

Directions

Open packet and use as a washcloth.

INACTIVE INGREDIENT

Ctric Acid, Alkyl Glucoside, Hydroxyethyl Cellulose, Nonoxynol-10, Glycerin, Sodium Hydroxide, Potassium Iodide, Purified Water.